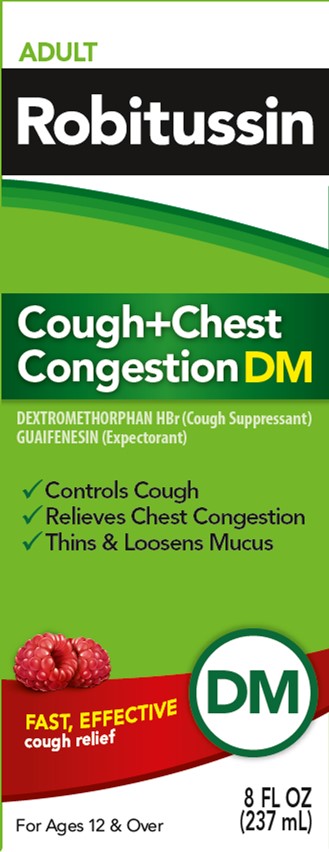 DRUG LABEL: ROBITUSSIN COUGH PLUS CHEST CONGESTION DM
NDC: 0031-8757 | Form: SOLUTION
Manufacturer: Haleon US Holdings LLC
Category: otc | Type: HUMAN OTC DRUG LABEL
Date: 20240408

ACTIVE INGREDIENTS: DEXTROMETHORPHAN HYDROBROMIDE 20 mg/20 mL; GUAIFENESIN 200 mg/20 mL
INACTIVE INGREDIENTS: ANHYDROUS CITRIC ACID; CARBOXYMETHYLCELLULOSE SODIUM, UNSPECIFIED; FD&C BLUE NO. 1; FD&C RED NO. 40; GLYCERIN; DEXTROSE, UNSPECIFIED FORM; MENTHOL, UNSPECIFIED FORM; POLYETHYLENE GLYCOL, UNSPECIFIED; PROPYLENE GLYCOL; WATER; SODIUM BENZOATE; SODIUM CITRATE, UNSPECIFIED FORM; SODIUM GLUCONATE; SUCRALOSE; TRIACETIN; XANTHAN GUM

Drug Facts

Active ingredients (in each 20 mL)

Dextromethorphan HBr, USP 20 mg

Guaifenesin, USP 200 mg

Purposes

Cough suppressant

Expectorant

Uses

- temporarily relieves cough due to minor throat and bronchial irritation as may occur with a cold
- helps loosen phlegm (mucus) and thin bronchial secretions to drain bronchial tubes

Warnings

DO NOT USE

Do not useif you are now taking a prescription monoamine oxidase inhibitor (MAOI) (certain drugs for depression, psychiatric, or emotional conditions, or Parkinson's disease), or for 2 weeks after stopping the MAOI drug. If you do not know if your prescription drug contains an MAOI, ask a doctor or pharmacist before taking this product.

Ask a doctor before use if you have

- cough that occurs with too much phlegm (mucus)
- cough that lasts or is chronic such as occurs with smoking, asthma, chronic bronchitis, or emphysema

Stop use and ask a doctor ifcough lasts more than 7 days, comes back, or is accompanied by fever, rash, or persistent headache. These could be signs of a serious condition.

PREGNANCY OR BREAST FEEDING

If pregnant or breast-feeding,ask a health professional before use.

Keep out of reach of children.In case of overdose, get medical help or contact a Poison Control Center right away.

Directions

- do not take more than 6 doses in any 24-hour period
- measure only with dosing cup provided
- keep dosing cup with product
- mL = milliliter
- this adult product is not intended for use in children under 12 years of age

age | dose
adults and children 12 years and over | 20 mL every 4 hours
children under 12 years | do not use

Other information

- each 20 mL contains:sodium 20 mg
- store at 20-25°C (68-77°F). Do not refrigerate.

Inactive ingredients

anhydrous citric acid, carboxymethylcellulose sodium, FD&C blue no. 1, FD&C red no. 40, glycerin, liquid glucose, menthol, natural and artificial flavors, polyethylene glycol, propylene glycol, purified water, sodium benzoate, sodium citrate, sodium gluconate, sucralose, triacetin, xanthan gum

Questions or comments?

call weekdays from 9 AM to 5 PM EST at 1-800-245-1040

Additional Information

Do Not Use if foil is missing or broken.

PARENTS:

Learn about teen medicine abuse

www.StopMedicineAbuse.org

Use dosage cup included

Distributed by:

GSK Consumer Healthcare, Warren, NJ 07059

For most recent product information,

visit www.robitussin.com

Trademarks are owned by or licensed to the GSK group of companies.

@2023 GSK group of companies or its licensor.

202887 Front Carton

PRINCIPAL DISPLAY PANEL

ADULT

Robitussin

Cough+Chest
Congestion DM

DEXTROMETHORPHAN HBr (Cough Suppressant)
GUAIFENESIN (Expectorant)

- Controls Cough
- Relieves Chest Congestion
- Thins & Loosens Mucus

FAST, EFFECTIVE
cough relief

DM

For Ages 12 & Over
8 FL OZ (237 mL)